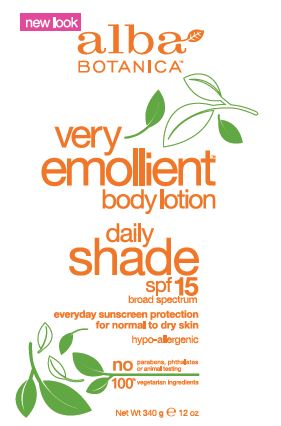 DRUG LABEL: Very Emollient Body Daily Shade SPF15
NDC: 61995-0371 | Form: LOTION
Manufacturer: The Hain Celestial Group
Category: otc | Type: HUMAN OTC DRUG LABEL
Date: 20240731

ACTIVE INGREDIENTS: HOMOSALATE 7.5 g/100 g; OCTISALATE 5 g/100 g; OCTOCRYLENE 3 g/100 g; AVOBENZONE 2 g/100 g
INACTIVE INGREDIENTS: POLYSORBATE 60; JOJOBA OIL; DEHYDROACETIC ACID; LECITHIN, SOYBEAN; LACTIC ACID; ALCOHOL; BUTYLPHENYL METHYLPROPIONAL; ECHINACEA ANGUSTIFOLIA; SAFFLOWER OIL; CETYL ALCOHOL; DIMETHICONE 100; ALOE VERA LEAF; GREEN TEA LEAF; COUMARIN; GLYCERYL STEARATE SE; BENZYL ALCOHOL; HYDROXYISOHEXYL 3-CYCLOHEXENE CARBOXALDEHYDE; LAVANDULA ANGUSTIFOLIA WHOLE; SHEA BUTTER; HYDROGENATED PALM KERNEL OIL; PHENOXYETHANOL; XANTHAN GUM; GRAPE SEED OIL; PANTHENOL; GLYCOLIC ACID; ALLANTOIN; LIMONENE, (+/-)-; AVOCADO OIL; GLYCERIN; WATER; SESAME OIL; POTASSIUM HYDROXIDE; ASCORBIC ACID; .ALPHA.-HEXYLCINNAMALDEHYDE, (2E)-; .ALPHA.-AMYLCINNAMALDEHYDE; GERANIOL; LINALOOL, (+/-)-; BENZYL SALICYLATE; MATRICARIA CHAMOMILLA; CUCUMBER; POTASSIUM SORBATE; SODIUM BENZOATE

Very Emollient Daily Shade SPF 15

ACTIVE INGREDIENT

Avobenzone 2.5%

Homosalate 7.5%

Octisalate 5.0%

Octocrylene 3.0%

PURPOSE

Sunscreen

Keep out of reach of children. If swallowed, get medical help or contact a Poison Control Center right away.

INDICATIONS AND USAGE

For sunscreen use, apply liberally 15 minutes before sun exposure. Reapply at least every 2 hours. Use water resistant sunscreen when swimming or sweating. Children under 6 months: ask a doctor. Sun Protection Measures: Spending time in the sun increases your risk of skin cancer and early skin aging. To decrease risk, regularly use a sunscreen with Broad Spectrum SPF 15 or higher and other protective measures, including: limit time in sun, especially 10am-2pm, and wear long-sleeved shirts, pants, hats and sunglasses.

WARNINGS

For external use only. Do not use on damaged or broken skin. When using this product, keep out of eyes. Rinse with water to remove. Stop use and ask a doctor if skin rash occurs.

DOSAGE AND ADMINISTRATION

For sunscreen use, apply liberally 15 minutes before sun exposure. Reapply at least every 2 hours. Use water resistant sunscreen when swimming or sweating. Children under 6 months: ask a doctor.

INACTIVE INGREDIENT

Water (Aqua), Glycerin, Glyceryl Stearate SE, Carthamus Tinctorius (Safflower) Seed Oil, Cetyl Alcohol, Dimethicone, Cetearyl Alcohol, Sesamum Indicum (Sesame) Seed Oil, Butyrospermum Parkii (Shea) Butter, Persea Gratissima (Avocado) Oil, Simmondsia Chinensis (Jojoba) Seed Oil (1), Vitis Vinifera (Grape) Seed Oil, Aloe Barbadensis Leaf Juice (1), Camellia Sinensis Leaf Extract (1), Chamomilla Recutita (Matricaria) Flower Extract (1), Cucumis Sativus (Cucumber) Fruit Extract, Echinacea Angustifolia Extract (1), Lavandula Angustifolia (Lavender) Flower/Leaf/Stem Extract (1), Ascorbic Acid, Panthenol, Tocopheryl Acetate, Allantoin, Citric Acid, Glycolic Acid, Lactic Acid, Lecithin, Polysorbate 60, Potassium Hydroxide, Xanthan Gum, Alcohol (1), Benzoic Acid, Dehydroacetic Acid, Phenoxyethanol, Potassium Sorbate, Sodium Benzoate, Amyl Cinnamal, Benzyl Alcohol, Benzyl Salicylate, Butylphenyl Methylpropional, Coumarin, Geraniol, Hexyl Cinnamal, Limonene, Linalool, Fragrance (Parfum)